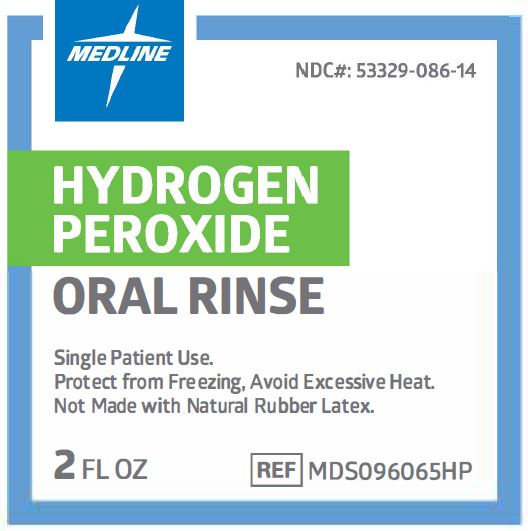 DRUG LABEL: Medline Peroxi Fresh
NDC: 53329-086 | Form: MOUTHWASH
Manufacturer: Medline Industries, LP
Category: otc | Type: HUMAN OTC DRUG LABEL
Date: 20241126

ACTIVE INGREDIENTS: HYDROGEN PEROXIDE 15 mg/1 mL
INACTIVE INGREDIENTS: SODIUM LAURYL SULFATE; SACCHARIN SODIUM; WATER

086 Medline Peroxi Fresh

Active ingredient

Hydrogen Peroxide 1.5%

Purpose

Oral Debriding Agent

Use

- aids in the removal of phlegm, mucus, or other secretions associated with occasional sore mouth

Warnings

Do not use this product

- for more than 7 days unless directed by a dentist or physician.

When using this product

- do not swallow

Stop use and ask a doctor if

- sore mouth symptoms do not improve in 7 days
- irritation, pain or redness persists or worsens
- swelling, rash or fever develops

Keep out of reach of children

- If more than used for rinsing is accidentally swallowed, get medical help or contact a poison Control Center right away.

Directions

- Adults and Children 2 Years of Age or Over: Swish around in mouth over affected area for at least 1 minute and then spit out. Use up to 4 times daily after meals and at bedtime or as directed by a dentist or doctor.
- Children Under 12 Years of Age: Should be supervised in the use of this product.
  Children Under 2 Years of Age: Consult a dentist or a doctor.

Other information

- avoid excessive heat and protect from freezing

Inactive ingredients

flavor, sodium lauryl sulfate, sodium saccharin, water

Manufacturing Information

Manufactured for:

Medline Industries, LP

Three Lakes Drive, Northfield, IL 60093 USA

Made in USA

www.medline.com

1-800-MEDLINE (633-5463)

REF: MDS096065HP

V1 RB22ANO